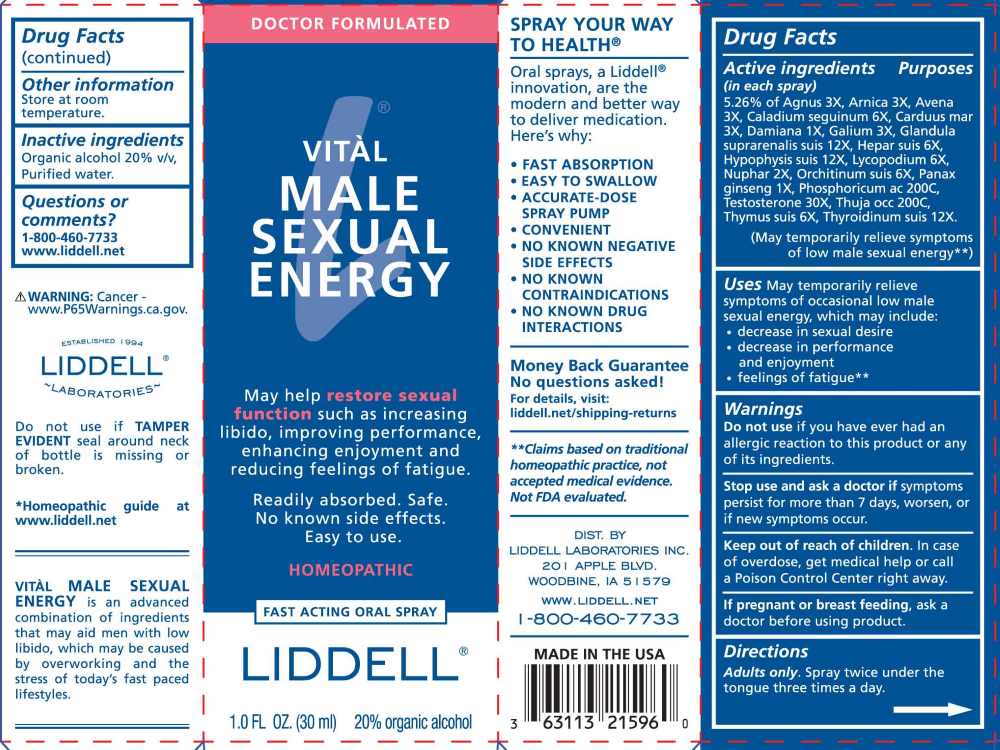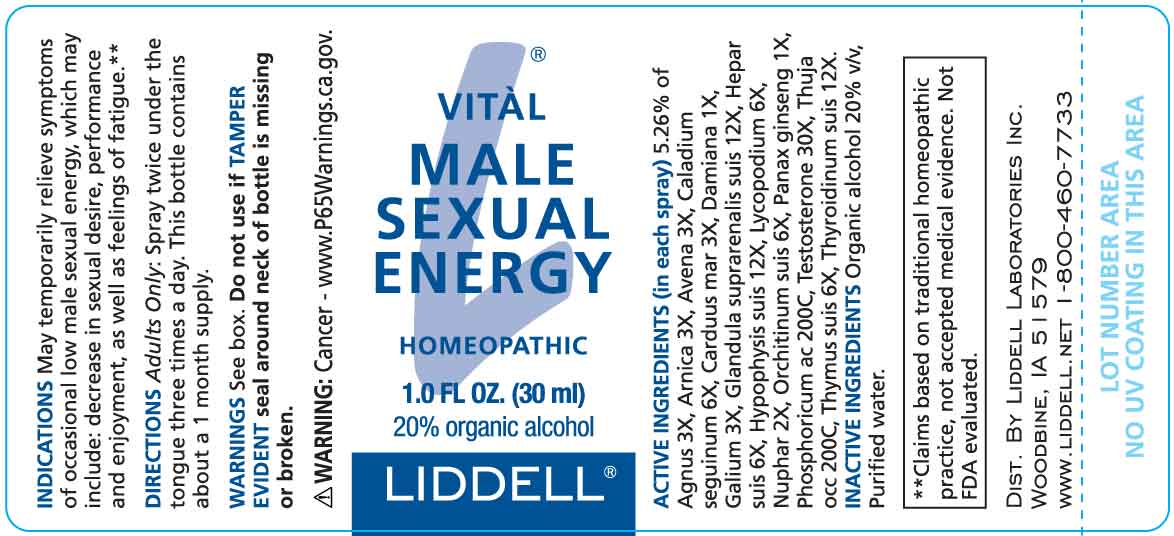 DRUG LABEL: Vital Male Sexual Energy
NDC: 50845-0286 | Form: SPRAY
Manufacturer: Liddell Laboratories, Inc.
Category: homeopathic | Type: HUMAN OTC DRUG LABEL
Date: 20260129
DEA Schedule: CIII

ACTIVE INGREDIENTS: CHASTE TREE FRUIT 3 [hp_X]/1 mL; ARNICA MONTANA WHOLE 3 [hp_X]/1 mL; AVENA SATIVA FLOWERING TOP 3 [hp_X]/1 mL; DIEFFENBACHIA SEGUINE WHOLE 6 [hp_X]/1 mL; MILK THISTLE 3 [hp_X]/1 mL; TURNERA DIFFUSA LEAFY TWIG 1 [hp_X]/1 mL; GALIUM APARINE WHOLE 3 [hp_X]/1 mL; SUS SCROFA ADRENAL GLAND 12 [hp_X]/1 mL; PORK LIVER 6 [hp_X]/1 mL; SUS SCROFA PITUITARY GLAND 12 [hp_X]/1 mL; LYCOPODIUM CLAVATUM SPORE 6 [hp_X]/1 mL; NUPHAR LUTEA ROOT 2 [hp_Q]/1 mL; SUS SCROFA TESTICLE 6 [hp_X]/1 mL; ASIAN GINSENG 1 [hp_X]/1 mL; PHOSPHORIC ACID 200 [hp_C]/1 mL; TESTOSTERONE 30 [hp_X]/1 mL; THUJA OCCIDENTALIS LEAFY TWIG 200 [hp_C]/1 mL; SUS SCROFA THYMUS 6 [hp_X]/1 mL; THYROID 12 [hp_X]/1 mL
INACTIVE INGREDIENTS: WATER; ALCOHOL

DRUG FACTS:

ACTIVE INGREDIENTS:

(in each spray) 5.26% of Agnus Castus 3X, Arnica Montana 3X, Avena Sativa 3X, Caladium Seguinum 6X, Carduus Marianus 3X, Damiana 1X, Galium Aparine 3X, Glandula Suprarenalis Suis 12X, Hepar Suis 6X, Hypophysis Suis 12X, Lycopodium Clavatum 6X, Nuphar Luteum 2X, Orchitinum Suis 6X, Panax Ginseng 1X, Phosphoricum Acidum 200C, Testosterone 30X, Thuja Occidentalis 200C, Thymus Suis 6X, Thyroidinum Suis 12X.

PURPOSE:

May temporarily relieve symptoms of occasional low male sexual energy, which may include: decrease in sexual desire, performance and enjoyment, as well as feelings of fatigue.**

**Claims based on traditional homeopathic practice, not accepted medical evidence. Not FDA evaluated.

WARNINGS:

Do not use if you have ever had an allergic reaction to this product or any of its ingredients.

Stop use and ask a doctor if symptoms persist for more than 7 days, worsen, or if new symptoms occur.

Keep out of reach of children. In case of overdose, get medical help or call a Poison Control Center right away.

If pregnant or breast feeding, ask a doctor before using product.

Do not use if TAMPER EVIDENT seal around neck of bottle is missing or broken.

Store at room temperature.

WARNING: Cancer - www.P65Warnings.ca.gov.

KEEP OUT OF REACH OF CHILDREN:

In case of overdose, get medical help or call a Poison Control Center right away.

DIRECTIONS:

Adults only: Spray twice under the tongue three times a day.

This bottle contains about a 1 month supply.

USES:

May temporarily relieve symptoms of occasional low male sexual energy, which may include:

• decrease in sexual desire

• decrease in performance and enjoyment

• feeling of fatigue**

**Claims based on traditional homeopathic practice, not accepted medical evidence. Not FDA evaluated.

INACTIVE INGREDIENTS:

Organic alcohol 20% v/v, Purified water.

QUESTIONS:

DIST. BY

LIDDELL LABORATORIES, INC.

201 APPLE BLVD.

WOODBINE, IA 51579

WWW.LIDDDELL.NET

1-800-460-7733

PACKAGE LABEL DISPLAY:

DOCTOR FORMULATED

VITÀL MALE SEXUAL ENERGY

May help restore sexual

function such as increasing

libido, improving performance,

enhancing enjoyment and

reducing feelings of fatigue.

Readily absorbed. Safe.

No known side effects.

Easy to use.

HOMEOPATHIC

FAST ACTING ORAL SPRAY

LIDDELL

1.0 FL OZ (30 ml)